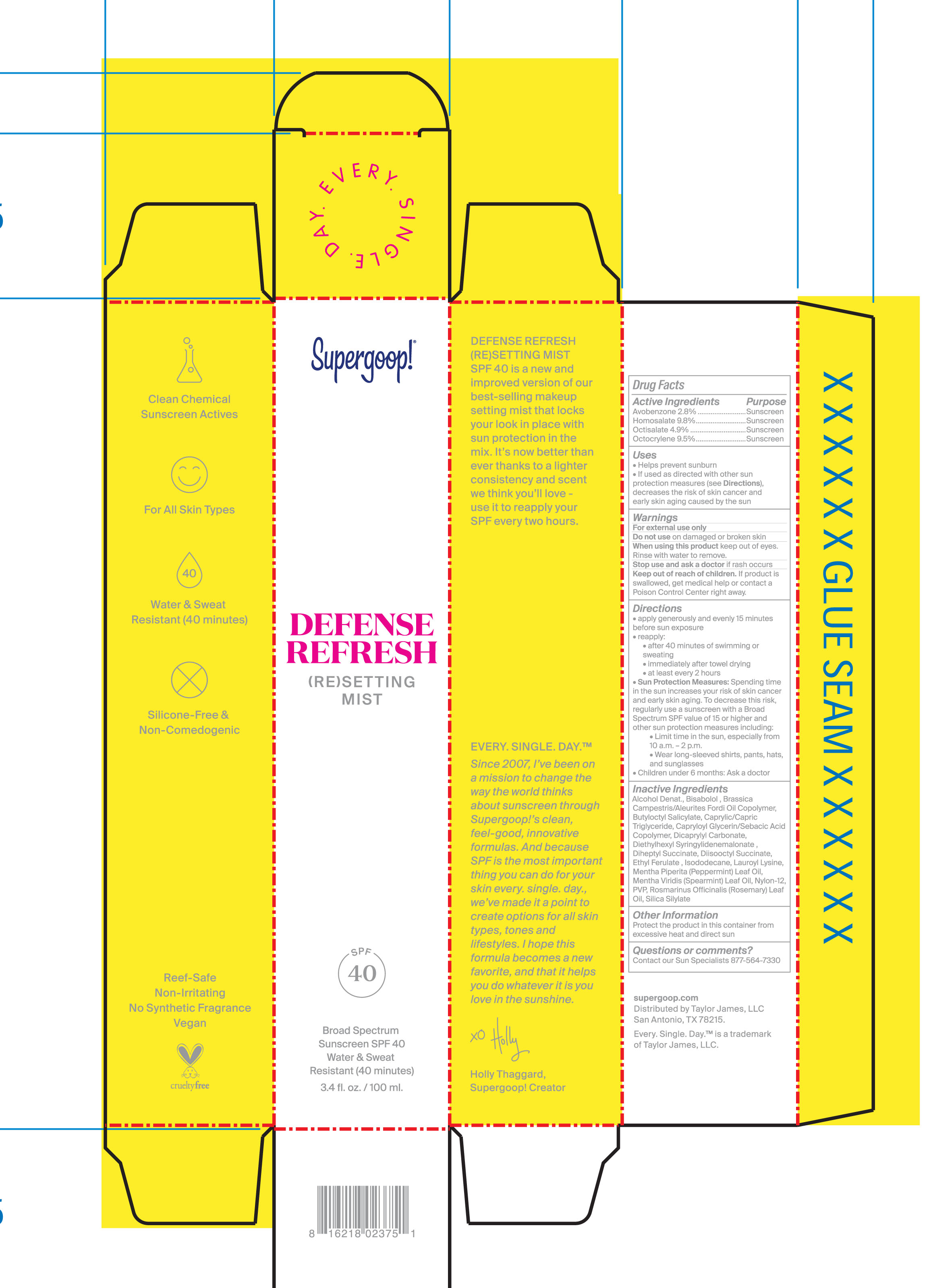 DRUG LABEL: Defense Refresh Setting Mist Broad Spectrum Sunscreen SPF 50
NDC: 75936-134 | Form: LIQUID
Manufacturer: Taylor James, LTD
Category: otc | Type: HUMAN OTC DRUG LABEL
Date: 20211021

ACTIVE INGREDIENTS: AVOBENZONE 2.8 g/100 mL; HOMOSALATE 9.8 g/100 mL; OCTISALATE 4.9 g/100 mL; OCTOCRYLENE 9.5 g/100 mL
INACTIVE INGREDIENTS: ALCOHOL; BUTYLOCTYL SALICYLATE; MEDIUM-CHAIN TRIGLYCERIDES; DICAPRYLYL CARBONATE; ISODODECANE; PEPPERMINT OIL; SPEARMINT OIL; ROSEMARY OIL; LEVOMENOL; CAPRYLOYL GLYCERIN/SEBACIC ACID COPOLYMER (2000 MPA.S); DIETHYLHEXYL SYRINGYLIDENEMALONATE; DIHEPTYL SUCCINATE; ETHYL FERULATE; LAUROYL LYSINE; NYLON-12

Defense Refresh Setting Mist Broad Spectrum Sunscreen SPF 50

Active Ingredients Purpose

Avobenzone 2.8% Sunscreen

Homosalate 9.8% Sunscreen

Octisalate 4.9% Sunscreen

Octocrylene 9.5% Sunscreen

Uses

Helps prevent sunburn

If used as directed with other sun protection measures (see Directions), decreases the risk of skin cancer and early skin aging caused by the sun.

Keep out of reach of children

If product is swallowed, get medical help or contact a Poison Control Center right away

Stop use and ask a doctor if rash occurs

Warnings For external Use only

Do not use on damaged or broken skin

When using this product keep out of eyes

Rinse with water to remove

Directions

Apply generously and evenly15 minutes before sun exposure

Reapply:

- after 40 minutes of swimming or sweating

- immediately after towel drying

- at least every 2 hours

Sun Protection Measures: Spending time in the sun increases your risk of early skin cancer and early skin aging. To decrease this risk, regularly use a sunscreen with a Broad Spectrum SPF calue of 15 or higher and other sun protection measures including:

- Limit time in the sun, especially from 10 a.m.-2p.m.

- Wear long-sleeved shirts, pants, hats, and sunglasses

Reapply at least every 2 hours

- Children under 6 months: Ask a doctor

INACTIVE INGREDIENT

Inactive Ingredients Alcohol Denat., Bisabolol, Brassica Compestris/Aleurites Fordi Oil Copolymer, Butyloctyl Salicylate, Caprylic/Capric Triglyceride, Capryloyl Glycerin/Sebacic Acid Copolymer, Dicaprylyl Carbonate, Diethylhexyl syringlidenemalonate, Diheptyl Succinate, Ethyl Ferulate, Isododecane, Lauroyl Lysine, Mentha Piperita (Peppermint) Stem/leaf Oil, Mentha Viridis (Spearmint) Leaf Oil, Nylon-12, PVP, Rosmarinus Officinalis (Rosemary) Leaf Oil, Silica Silylate

PACKAGE LABEL

Supergoop!

Defense (RE) Setting Mist

SPF 40

Broad Spectrum Sunscreen SPF 40

Water and Sweat Resistant (40 minutes)